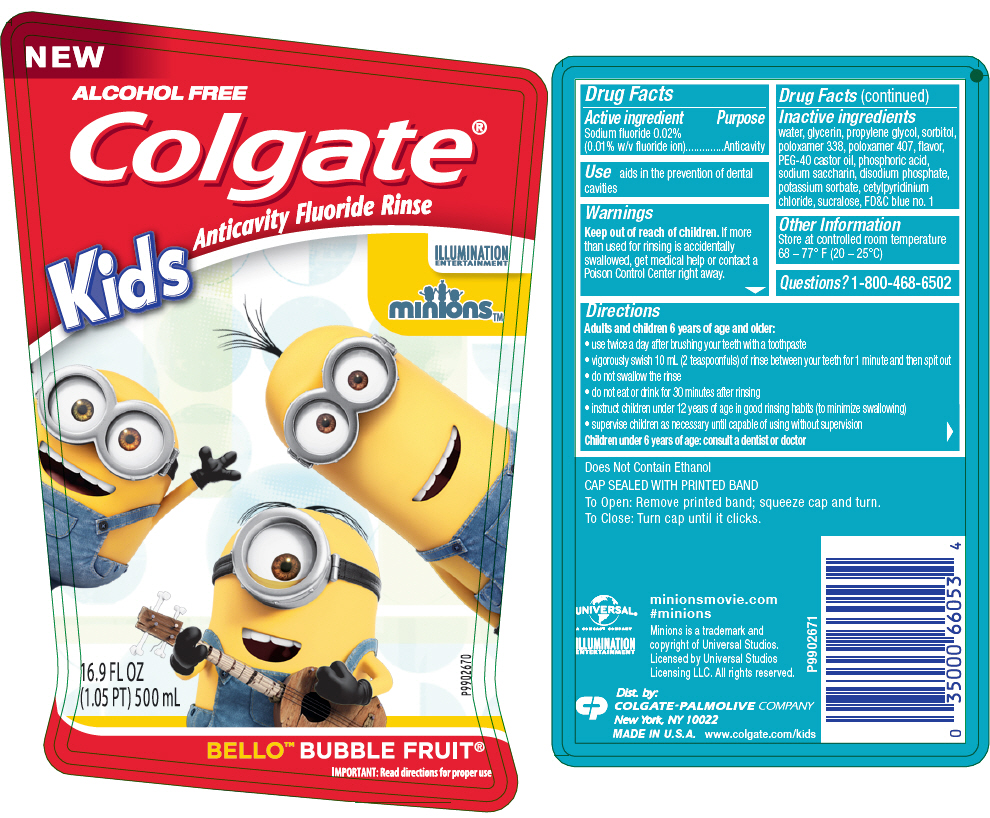 DRUG LABEL: Colgate Kids Minions Mouthwash
NDC: 35000-727 | Form: RINSE
Manufacturer: Colgate-Palmolive Company
Category: otc | Type: HUMAN OTC DRUG LABEL
Date: 20250219

ACTIVE INGREDIENTS: SODIUM FLUORIDE 0.1 mg/1 mL
INACTIVE INGREDIENTS: WATER; GLYCERIN; PROPYLENE GLYCOL; SORBITOL; POTASSIUM SORBATE; CETYLPYRIDINIUM CHLORIDE; SACCHARIN SODIUM; SUCRALOSE; POLOXAMER 407; POLOXAMER 338; SODIUM PHOSPHATE, DIBASIC, ANHYDROUS; PEG-40 CASTOR OIL; PHOSPHORIC ACID; FD&C BLUE NO. 1

Colgate® Kids Minions™ Mouthwash

Drug Facts

Active ingredient

Sodium fluoride 0.02% (0.01% w/v fluoride ion)

Purpose

Anticavity

Use

aids in the prevention of dental cavities

Warnings

Keep out of reach of children. If more than used for rinsing is accidentally swallowed, get medical help or contact a Poison Control Center right away.

Directions

Adults and children 6 years of age and older:

- use twice a day after brushing your teeth with a toothpaste
- vigorously swish 10 mL (2 teaspoonfuls) of rinse between your teeth for 1 minute and then spit out
- do not swallow the rinse
- do not eat or drink for 30 minutes after rinsing
- instruct children under 12 years of age in good rinsing habits (to minimize swallowing)
- supervise children as necessary until capable of using without supervision

Children under 6 years of age: consult a dentist or doctor

Inactive ingredients

water, glycerin, propylene glycol, sorbitol, poloxamer 338, poloxamer 407, flavor, PEG-40 castor oil, phosphoric acid, sodium saccharin, disodium phosphate, potassium sorbate, cetylpyridinium chloride, sucralose, FD&C blue no. 1

Other Information

Store at controlled room temperature 68 – 77° F (20 – 25°C)

Questions?

1-800-468-6502

Dist. by:
COLGATE-PALMOLIVE COMPANY
New York, NY 10022

PRINCIPAL DISPLAY PANEL - 500 mL Bottle Label

NEW

ALCOHOL FREE

Colgate®

Kids Anticavity Fluoride Rinse

ILLUMINATION
ENTERTAINMENT

minions™

16.9 FL OZ
(1.05 PT) 500 mL

P9902670

BELLO™ BUBBLE FRUIT®

IMPORTANT: Read directions for proper use